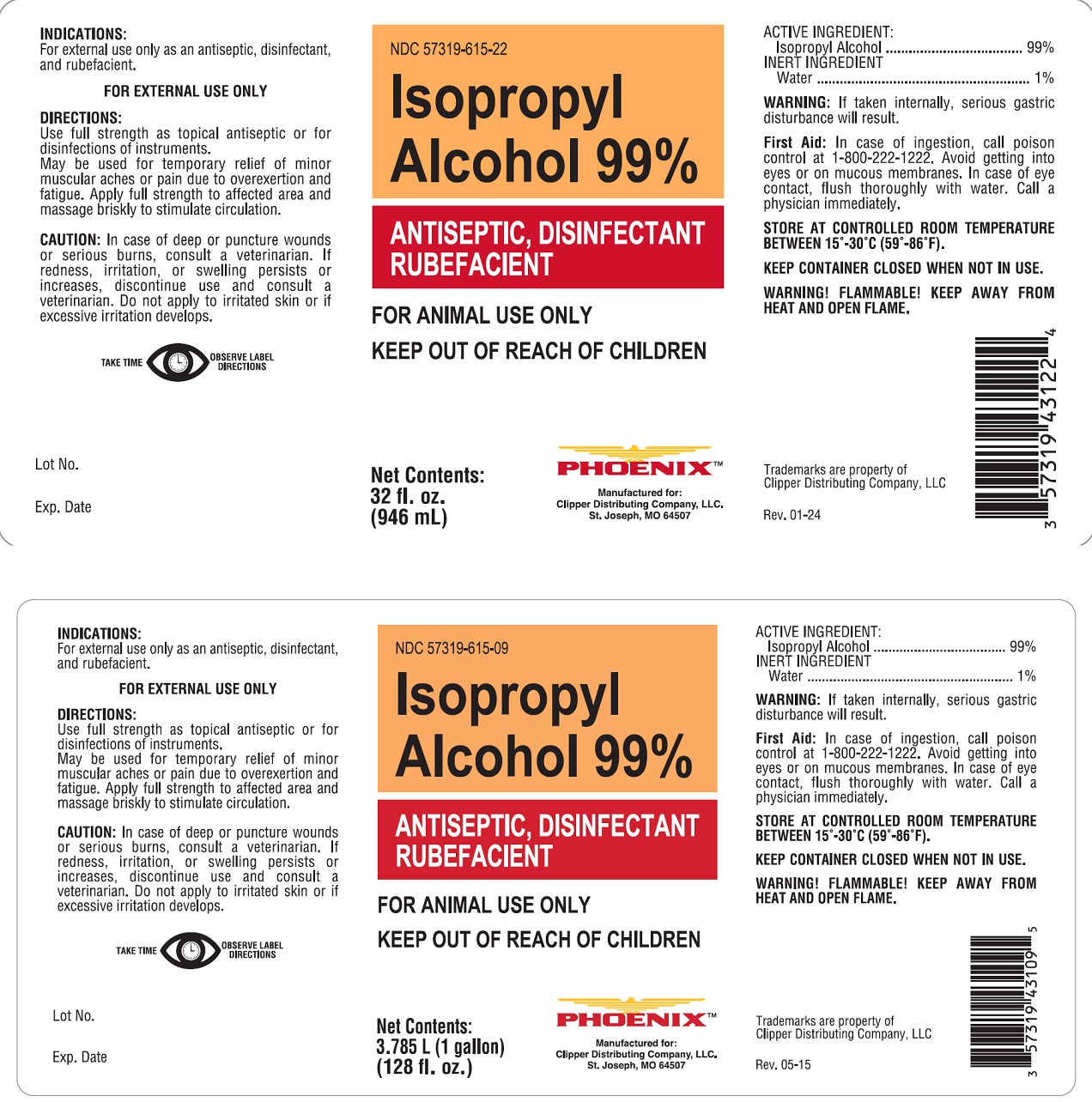 DRUG LABEL: ISOPROPYL ALCOHOL
NDC: 57319-615 | Form: LIQUID
Manufacturer: Phoenix
Category: animal | Type: OTC ANIMAL DRUG LABEL
Date: 20250129

ACTIVE INGREDIENTS: ISOPROPYL ALCOHOL 99 L/100 L

Isopropyl Alcohol 99%

WARNINGS AND PRECAUTIONS

Isopropyl Alcohol 99%

ANTISEPTIC, DISINFECTANT RUBEFACIENT

FOR ANIMAL USE ONLY

KEEP OUT OF REACH OF CHILDREN

FOR EXTERNAL USE ONLY

ACTIVE INGREDIENT:

Isopropyl Alcohol ...........................99%

INERT INGREDIENT:

Water ........................................... 1%

INDICATIONS: For external use only as an antiseptic, disinfectant, and rubefacient.

WARNING: If taken internally, serious gastric disturbance will result.

First Aid: In case of ingestion, call poison control at 1-800-222-1222. Avoid getting into eyes or on mucous membranes. In case of eye contact, flush thoroughly with water. Call a physician immediately.

STORE AT CONTROLLED ROOM TEMPERATURE BETWEEN 15°-30°C (59°-86°F)

KEEP CONTAINER CLOSED WHEN NOT IN USE

WARNING! FLAMMABLE!

KEEP AWAY FROM HEAT AND OPEN FLAME

DIRECTIONS: Use full strength as topical antiseptic or for disinfections of instruments. May be used for temporary relief of minor muscular aches or pain due to overexertion and fatigue. Apply full strength to affected area and massage briskly to stimulate circulation.

CAUTION: In case of deep or puncture wounds or serious burns, consult a veterinarian. If redness, irritation, or swelling persists or increases, discontinue use and consult a veterinarian. Do not apply to irritated skin or if excessive irritation develops.